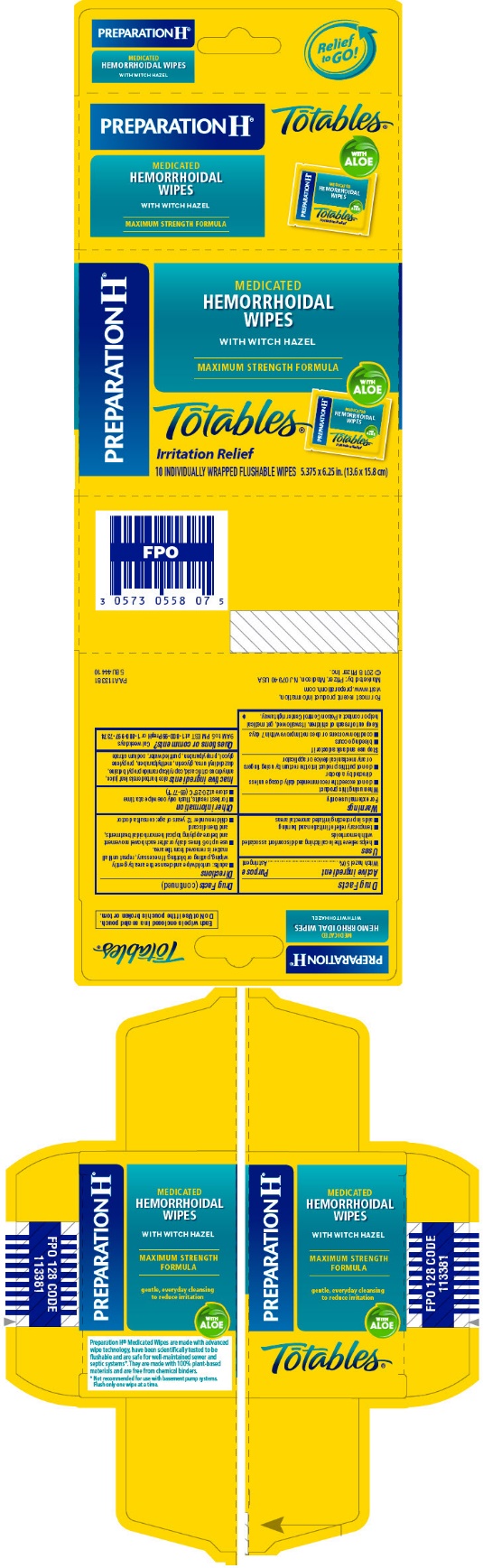 DRUG LABEL: PREPARATION H TOTABLES IRRITATION RELIEF WIPES
NDC: 0573-0558 | Form: CLOTH
Manufacturer: Haleon US Holdings LLC
Category: otc | Type: HUMAN OTC DRUG LABEL
Date: 20250221

ACTIVE INGREDIENTS: WITCH HAZEL 5 g/1 1
INACTIVE INGREDIENTS: ALOE VERA LEAF; ANHYDROUS CITRIC ACID; CAPRYL/CAPRAMIDOPROPYL BETAINE; DIAZOLIDINYL UREA; GLYCERIN; METHYLPARABEN; PROPYLENE GLYCOL; PROPYLPARABEN; SODIUM CITRATE, UNSPECIFIED FORM; WATER

Drug Facts

Active ingredient

Witch hazel 50%

Purpose

Astringent

Uses

- helps relieve the local itching and discomfort associated with hemorrhoids
- temporary relief of irritation and burning
- aids in protecting irritated anorectal areas

Warnings

For external use only

When using this product

- do not exceed the recommended daily dosage unless directed by a doctor
- do not put this product into the rectum by using fingers or any mechanical device or applicator

Stop use and ask a doctor if

- bleeding occurs
- condition worsens or does not improve within 7 days

Keep out of reach of children.If swallowed, get medical help or contact a Poison Control Center right away.

Directions

- adults: unfold wipe and cleanse the area by gently wiping, patting or blotting. If necessary, repeat until all matter is removed from the area.
- use up to 6 times daily or after each bowel movement and before applying topical hemorrhoidal treatments, and then discard
- children under 12 years of age: consult a doctor

Other information

- for best results, flush only one wipe at a time
- store at 20-25°C (68-77°F)

Inactive ingredients

aloe barbadensis leaf juice, anhydrous citric acid, capryl/capramidopropyl betaine, diazolidinyl urea, glycerin, methylparaben, propylene glycol, propylparaben, purified water, sodium citrate

Questions or comments?

Call weekdays 9 AM to 5 PM EST at 1-800-99PrepHor 1-800-997-7374.

For most recent product information, visit www.preparationh.com.

PRINCIPAL DISPLAY PANEL

PREPARATION H®

MEDICATED
HEMORRHOIDAL
WIPES

WITH WITCH HAZEL

MAXIMUM STRENGTH FORMULA

WITH
ALOE

Tōtables®

Irritation Relief

10 INDIVIDUALLY WRAPPED FLUSHABLE WIPES
5.375 x 6.25 in. (13.6 x 15.8 cm)